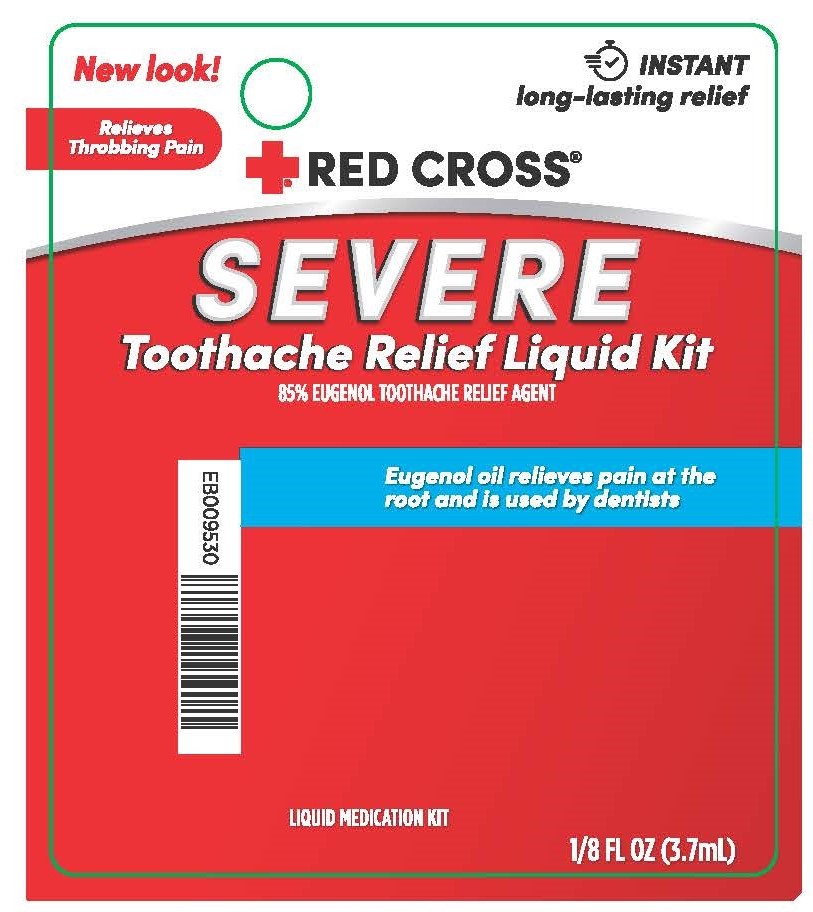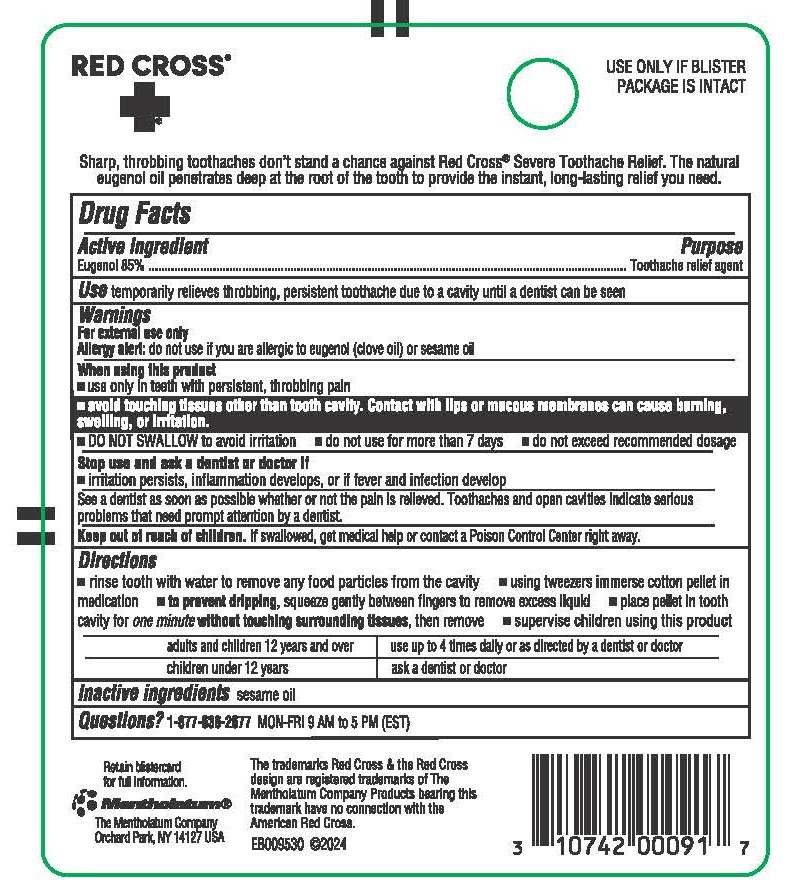 DRUG LABEL: Red Cross Toothache
NDC: 10742-0009 | Form: LIQUID
Manufacturer: The Mentholatum Company
Category: otc | Type: HUMAN OTC DRUG LABEL
Date: 20250611

ACTIVE INGREDIENTS: EUGENOL 850 mg/1 mL
INACTIVE INGREDIENTS: SESAME OIL

Drug Facts - Red Cross Toothache

Active ingredient

Eugenol 85%

Purpose

Toothache relief agent

Uses

temporarily relieves throbbing, persistent toothache due to a cavity until a dentist can be seen

Warnings

For external use only

Allergy alert: do not use if you are allergic to eugenol (clove oil)

When using this product

- use only in teeth with persistent, throbbing pain
- avoid touching tissues other than tooth cavity. Contact with lips or mucous membranes can cause burning, swelling, or irritation.
- DO NOT SWALLOW to avoid irritation
- do not use for more than 7 days
- do not exceed recommended dosage

Stop use and ask a dentist or doctor if

- irritation persists, inflammation develops, or if fever and infection develop

See a dentist as soon as possible whether or not the pain is relieved. Toothaches and open cavities indicate serious problems that need prompt attention by a dentist.

Keep Out of Reach of Children

If swallowed, get medical help or contact a Poison Control Center right away.

Directions

- rinse tooth with water to remove any food particles from the cavity
- using tweezers, immerse cotton pellet in medication
- to prevent dripping, squeeze gently between fingers to remove excess liquid
- place pellet in tooth cavity for one minutewithout touching surrounding tissues, then remove
- supervise children using this product

adults and children 12 years and over: use up to 4 times daily or as directed by a dentist or doctor

children under 12 years: ask a dentist or doctor

Inactive Ingredients

sesame oil

Questions

1-877-636-2677 MON-FRI 9 AM to 5 PM (EST)

Package Label/Principal Display Panel